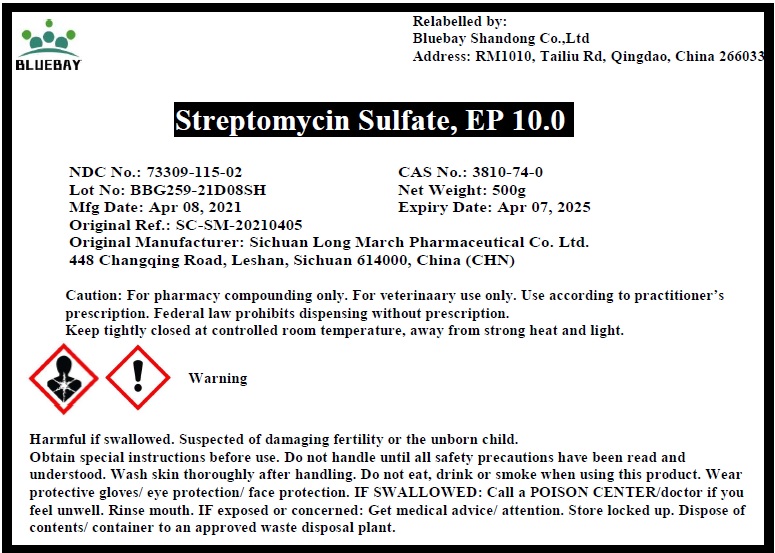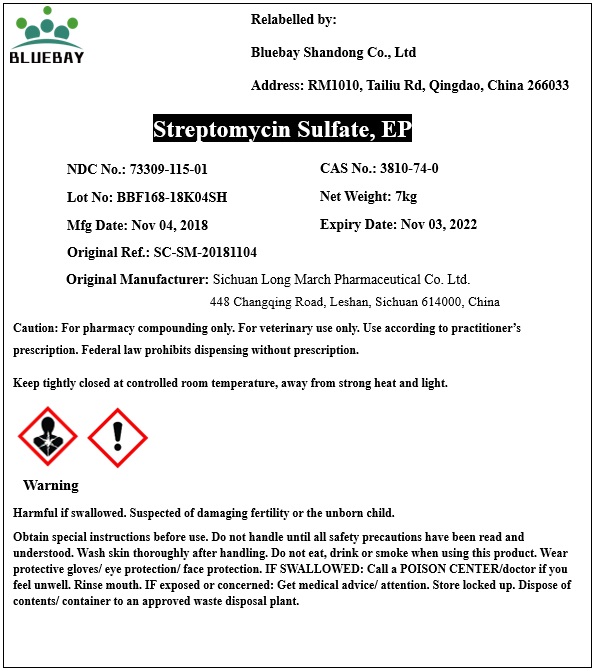 DRUG LABEL: Streptomycin Sulfate
NDC: 73309-115 | Form: POWDER
Manufacturer: BLUEBAY SHANDONG CO.,LTD
Category: other | Type: BULK INGREDIENT
Date: 20210521

ACTIVE INGREDIENTS: STREPTOMYCIN SULFATE 1 kg/1 kg

Streptomycin Sulfate